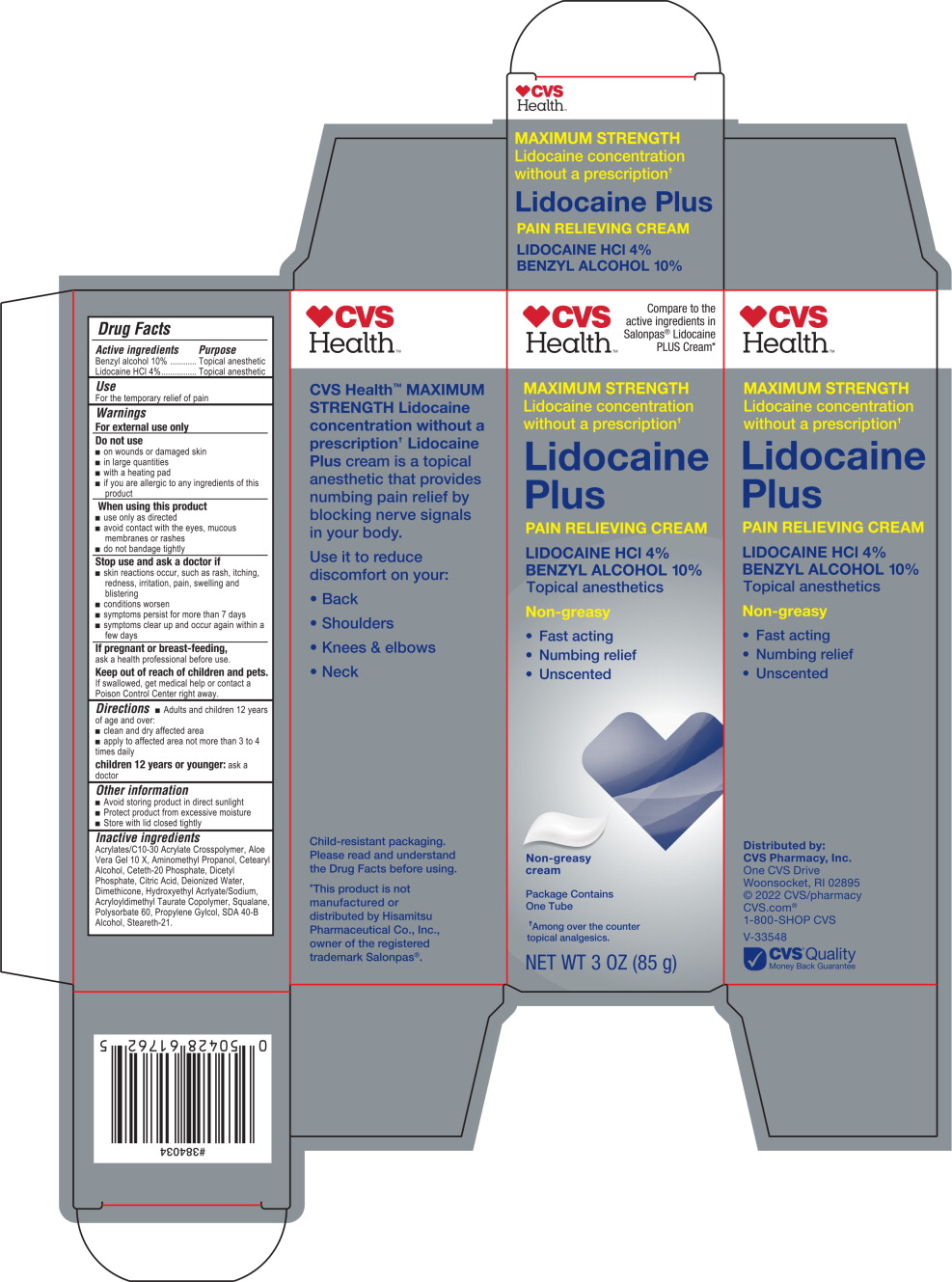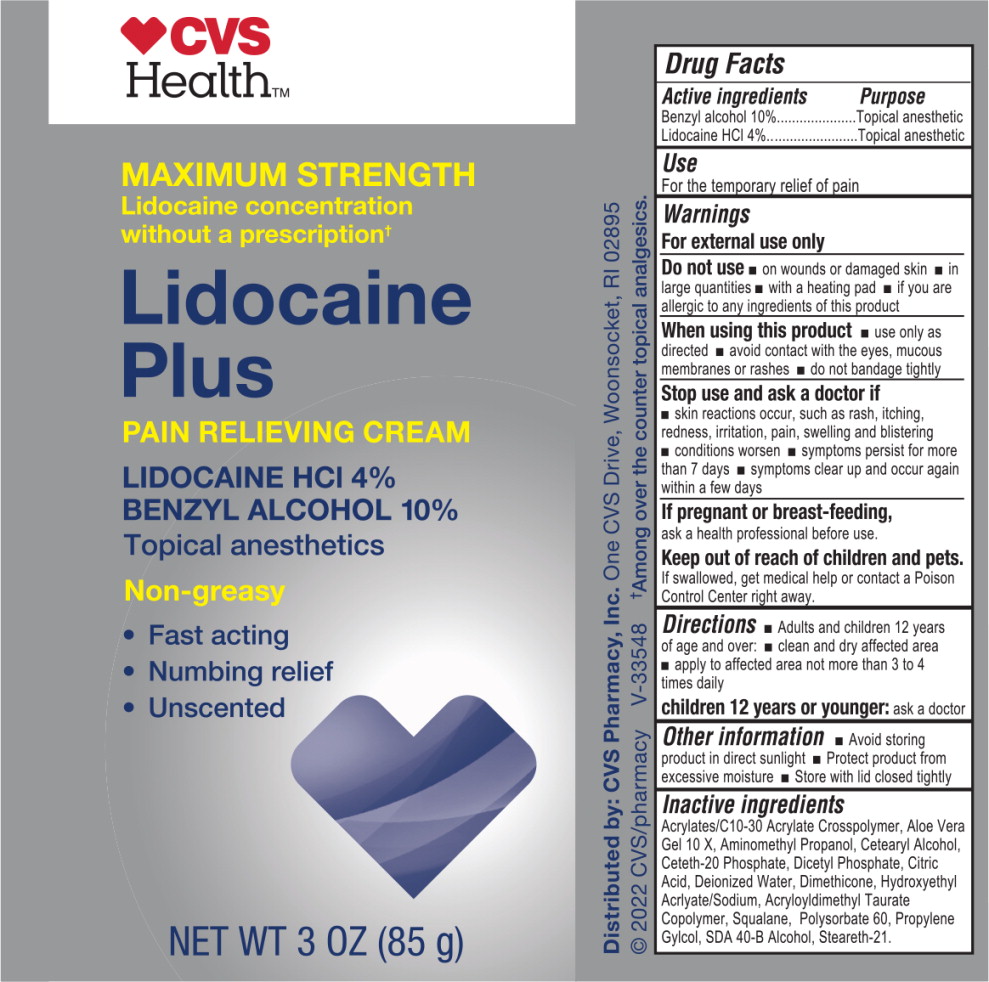 DRUG LABEL: CVS Health Lidocaine Plus
NDC: 66902-758 | Form: CREAM
Manufacturer: NATURAL ESSENTIALS, INC.
Category: otc | Type: HUMAN OTC DRUG LABEL
Date: 20241001

ACTIVE INGREDIENTS: LIDOCAINE HYDROCHLORIDE 40 mg/1 g; BENZYL ALCOHOL 100 mg/1 g
INACTIVE INGREDIENTS: CARBOMER COPOLYMER TYPE B (ALLYL PENTAERYTHRITOL CROSSLINKED); ALOE VERA LEAF; AMINOMETHYLPROPANOL; CETOSTEARYL ALCOHOL; CETETH-20 PHOSPHATE; DIHEXADECYL PHOSPHATE; CITRIC ACID MONOHYDRATE; WATER; DIMETHICONE; HYDROXYETHYL ACRYLATE/SODIUM ACRYLOYLDIMETHYL TAURATE COPOLYMER (100000 MPA.S AT 1.5%); SQUALENE; POLYSORBATE 60; PROPYLENE GLYCOL; ALCOHOL; STEARETH-21

Drug Facts

Active ingredients

Benzyl alcohol 10%

Lidocaine HCl 4%

Purpose

Topical anesthetic

Topical anesthetic

Use

For the temporary relief of pain

Warnings

For external use only

Do not use

- on wounds or damaged skin
- in large quantities
- with a heating pad
- if you are allergic to any ingredients of this product

When using this product

- use only as directed
- avoid contact with the eyes, mucous membranes or rashes
- do not bandage tightly

Stop use and ask a doctor if

- skin reactions occur, such as rash, itching, redness, irritation, pain, swelling and blistering
- conditions worsen
- symptoms persist for more than 7 days
- symptoms clear up and occur again within a few days

If pregnant or breast-feeding,

ask a health professional before use.

Keep out of reach of children and pets.

If swallowed, get medical help or contact a Poison Control Center right away.

Directions

- Adults and children 12 years of age and over:
- clean and dry affected area
- apply to affected area not more than 3 to 4 times daily

children 12 years or younger:ask a doctor

Other information

- Avoid storing product in direct sunlight
- Protect product from excessive moisture
- Store with lid closed tightly

Inactive ingredients

Acrylates/C10-30 Acrylate Crosspolymer, Aloe Vera Gel 10 X, Aminomethyl Propanol, Cetearyl Alcohol, Ceteth-20 Phosphate, Dicetyl Phosphate, Citric Acid, Deionized Water, Dimethicone, Hydroxyethyl Acrlyate/Sodium, Acryloyldimethyl Taurate Copolymer, Squalane, Polysorbate 60, Propylene Gylcol, SDA 40-B Alcohol, Steareth-21.

Principal-Display Panel – 85 g Carton Label

CVS
Health™

Compare to the
active ingredients in
Salonpas®Lidocaine
PLUS Cream*

MAXIMUM STRENGTH
Lidocaine concentration
without a prescription ✝

Lidocaine
Plus

PAIN RELIEVING CREAM

LIDOCAINE HCl 4%

BENZYL ALCOHOL 10%

Topical anesthetics

Non-greasy

- Fast acting
- Numbing relief
- Unscented

Non-greasy
cream

Package Contains
One Tube

✝Among over the counter
topical analgesics.

NET WT 3 0Z (85 g)

Principal-Display Panel – 85 g Carton Label

CVS
Health™

MAXIMUM STRENGTH
Lidocaine concentration
without a prescription ✝

Lidocaine
Plus

PAIN RELIEVING CREAM

LIDOCAINE HCl 4%

BENZYL ALCOHOL 10%

Topical anesthetics

Non-greasy

- Fast acting
- Numbing relief
- Unscented

NET WT 3 0Z (85 g)